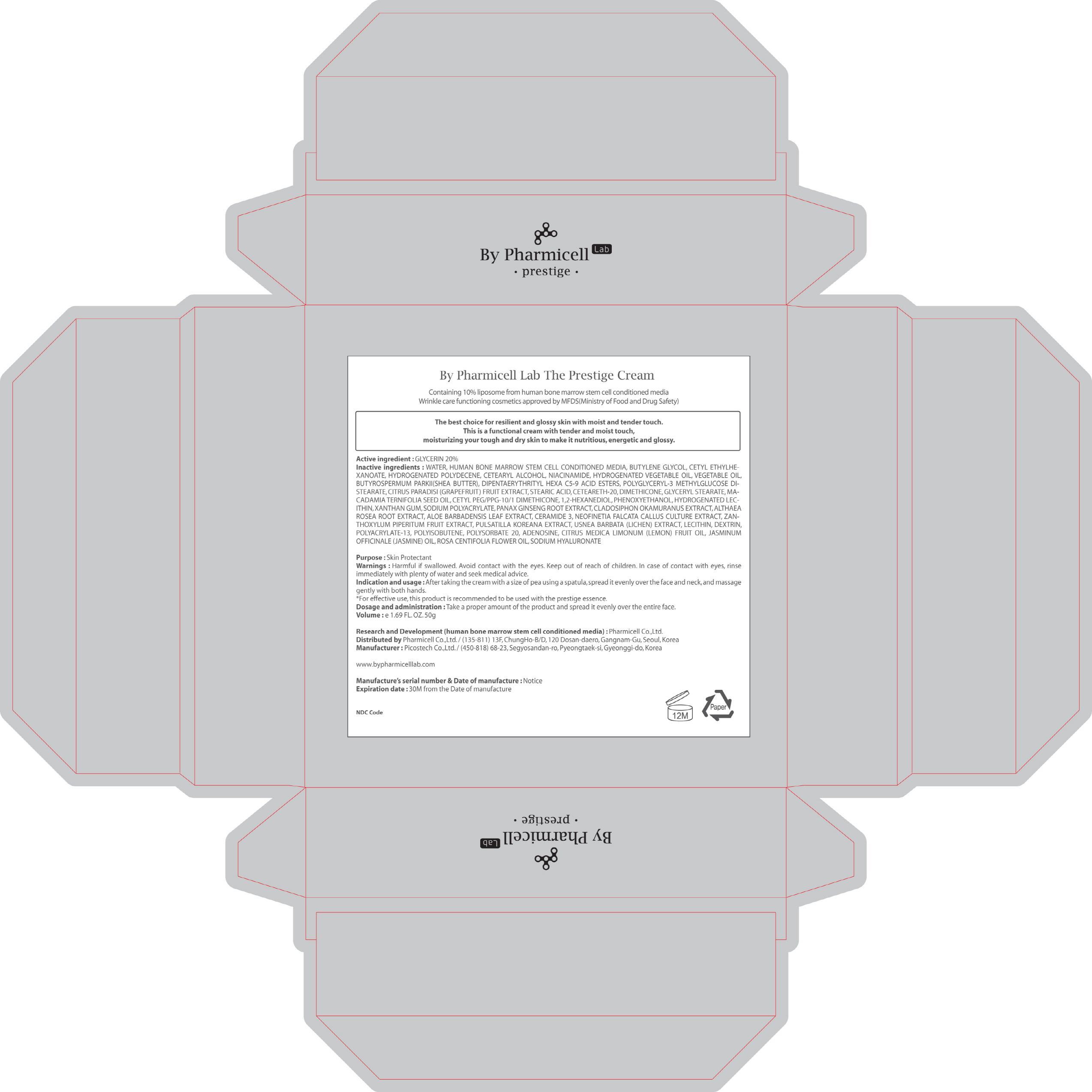 DRUG LABEL: The Prestige
NDC: 60949-180 | Form: CREAM
Manufacturer: Pharmicell Co., Ltd.
Category: otc | Type: HUMAN OTC DRUG LABEL
Date: 20140922

ACTIVE INGREDIENTS: GLYCERIN 10 g/50 g
INACTIVE INGREDIENTS: WATER; BUTYLENE GLYCOL

ACTIVE INGREDIENT

Active ingredient : GLYCERIN 20%

INACTIVE INGREDIENT

Inactive ingredients : WATER, HUMAN BONE MARROW STEM CELL CONDITIONED MEDIA, BUTYLENE GLYCOL, CETYL ETHYLHEXANOATE, HYDROGENATED POLYDECENE, CETEARYL ALCOHOL, NIACINAMIDE, HYDROGENATED VEGETABLE OIL, VEGETABLE OIL, BUTYROSPERMUM PARKII(SHEA BUTTER), DIPENTAERYTHRITYL HEXA C5-9 ACID ESTERS, POLYGLYCERYL-3 METHYLGLUCOSE DISTEARATE, CITRUS PARADISI (GRAPEFRUIT) FRUIT EXTRACT, STEARIC ACID, CETEARETH-20, DIMETHICONE, GLYCERYL STEARATE, MACADAMIA TERNIFOLIA SEED OIL, CETYL PEG/PPG-10/1 DIMETHICONE, 1,2-HEXANEDIOL, PHENOXYETHANOL, HYDROGENATED LECITHIN, XANTHAN GUM, SODIUM POLYACRYLATE, PANAX GINSENG ROOT EXTRACT, CLADOSIPHON OKAMURANUS EXTRACT, ALTHAEA ROSEA ROOT EXTRACT, ALOE BARBADENSIS LEAF EXTRACT, CERAMIDE 3, NEOFINETIA FALCATA CALLUS CULTURE EXTRACT, ZANTHOXYLUM PIPERITUM FRUIT EXTRACT, PULSATILLA KOREANA EXTRACT, USNEA BARBATA (LICHEN) EXTRACT, LECITHIN, DEXTRIN, POLYACRYLATE-13, POLYISOBUTENE, POLYSORBATE 20, ADENOSINE, CITRUS MEDICA LIMONUM (LEMON) FRUIT OIL, JASMINUM OFFICINALE (JASMINE) OIL, ROSA CENTIFOLIA FLOWER OIL, SODIUM HYALURONATE

PURPOSE

Purpose : Skin Protectant

WARNINGS

Warnings : Harmful if swallowed. Avoid contact with the eyes. Keep out of reach of children. In case of contact with eyes, rinse immediately with plenty of water and seek medical advice.

KEEP OUT OF REACH OF CHILDREN

INDICATIONS & USAGE

Indication and usage : After pumping a proper amount of the essence, spread it evenly along the lines of the face for sufficient absorption.
- For effective use, this product is recommended to be used with the prestige essence.

DOSAGE & ADMINISTRATION

Dosage and administration : Take a proper amount of the product and spread it evenly over the entire face.